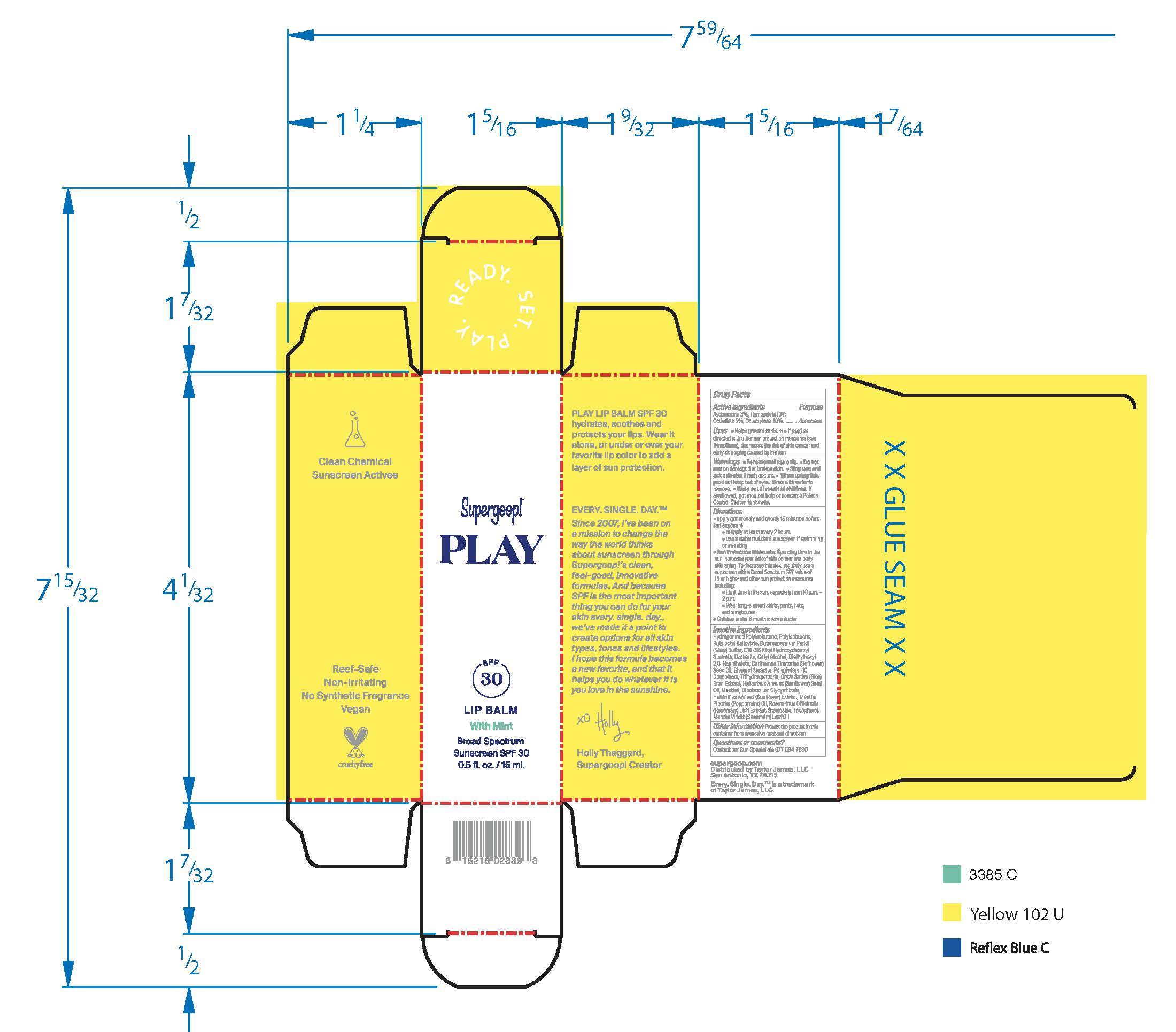 DRUG LABEL: Play Lip Balm Broad Spectrum SPF 30 with Mint
NDC: 75936-226 | Form: STICK
Manufacturer: Supergoop, LLC
Category: otc | Type: HUMAN OTC DRUG LABEL
Date: 20241204

ACTIVE INGREDIENTS: OCTISALATE 5 g/100 mL; OCTOCRYLENE 10 g/100 mL; AVOBENZONE 3 g/100 mL; HOMOSALATE 10 g/100 mL
INACTIVE INGREDIENTS: SHEA BUTTER; CERESIN; SAFFLOWER OIL; TRIHYDROXYSTEARIN; RICE BRAN; ROSEMARY; TOCOPHEROL; DIETHYLHEXYL 2,6-NAPHTHALATE; GLYCERYL MONOSTEARATE; SUNFLOWER OIL; GLYCYRRHIZINATE DIPOTASSIUM; PEPPERMINT OIL; STEVIOSIDE; MENTHA SPICATA OIL; POLYISOBUTYLENE (1300 MW); BUTYLOCTYL SALICYLATE; CETYL ALCOHOL; POLYGLYCERYL-10 DECAOLEATE; MENTHOL; HELIANTHUS ANNUUS FLOWERING TOP; HYDROGENATED POLYBUTENE (1300 MW)

Play Lip Balm Broad Spectrum SPF 30 with Mint

Active Ingredients Purpose

Avobenozone 3% Sunscreen

Homosalate 10% Sunscreen

Octisalate 5% Sunscreen

Octocrylene 10% Sunscreen

Uses
Helps Prevent Sunburn
If used as directed with other sun protection measures (see Directions), decreases the risk of skin cancer and early skin aging caused by the sun.

Keep out of reach of children.
If product is swallowed, get medical help or contact a poison Control Center right away

Stop use and ask a doctor if rash occurs.

Warnings

For external use only

Do not use on damaged or broken skin

When using this product keep out of eyes. Rinse with water to remove

Directions
Apply generously and evenly 15 minutes before sun exposure
Reapply at least every 2 hours.

Use a water-resistant sunscreen if swimming or sweating

Sun Protection Measures Spending time in the sun increases your risk of
skin cancer and early skin aging. To decrease this risk, regularly use a
sunscreen with a Broad-Spectrum SPF value of 15 or higher and other sun
protection measures including: • limit your time in the sun, especially from 10
a.m. – 2 p.m. • wear long-sleeved shirts, pants, hats, and sunglasses •
Children under 6 months of age: ask a doctor.

INACTIVE INGREDIENT

Hydrogenated Polyisobutene, Polyisobutene, Butylocyl Salicylate, Butyrospermum Parkii (Shea) Butter, C18-38 Alkyl Hydroxystearoyl Stearate, Ozokerite, Cetyl Alcohol, Diethylhexyl 2,6-Naphthalate, Carthamus Tinctorius (Safflower) Seed Oil, Glyceryl Stearate, Polyglyceryl-10 Decaoleate, Trihydroxystearin, Oryza Sativa (Rice) Bran Extract, Helianthus Annuus (Sunflower) Seed Oil, Menthol, Dipotassium Glycyrrhizate, Helianthus Annuus (Sunflower) Extract, Mentha Piperita (Peppermint) Oil, Rosmarinus Officinalis (Rosemary) Leaf Extract, Stevioside, Tocopherol, Mentha Viridis (Spearmint) Leaf Oil

PACKAGE LABEL

Supergoop!

PLAY SPF 30

LIP BALM with Mint

Broad Spectrum Sunscreen SPF 30

0.5 fl. oz./ 15 ml.